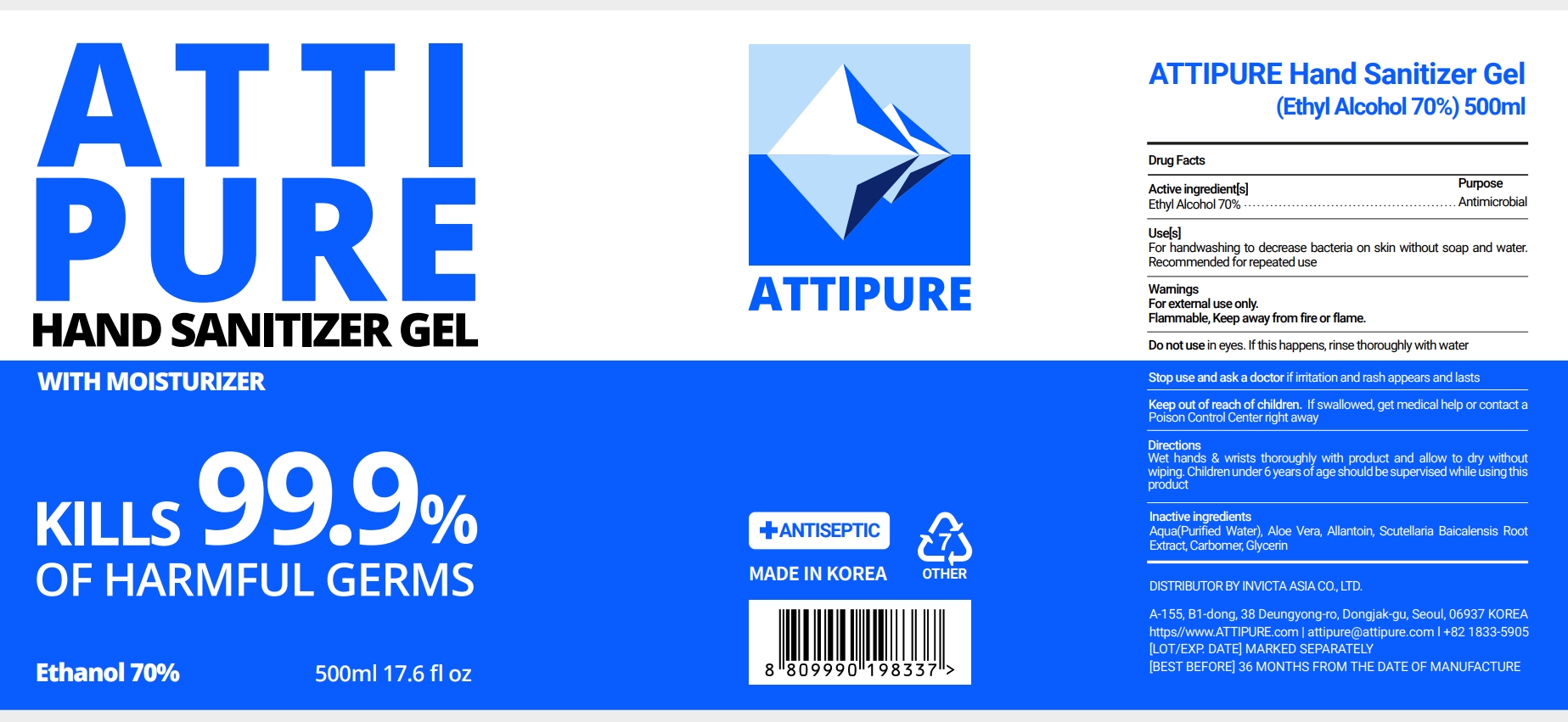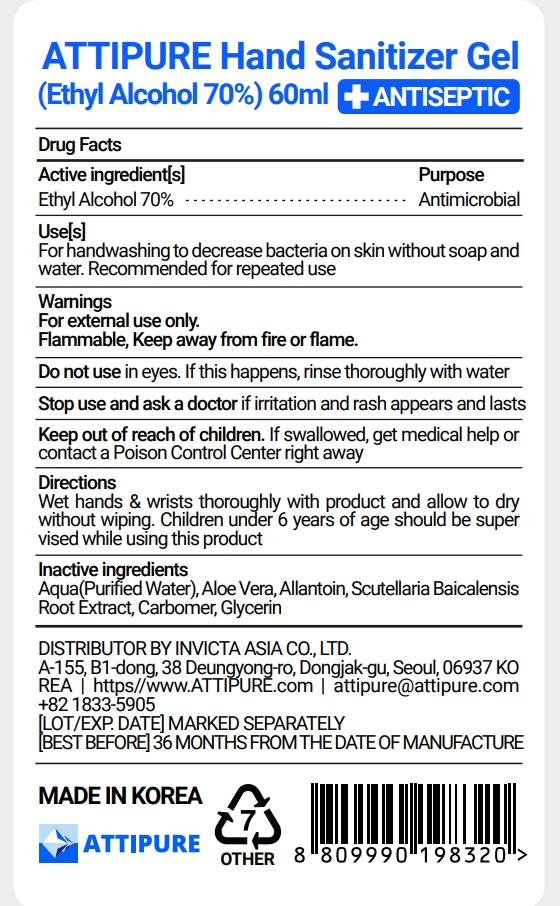 DRUG LABEL: ATTIPURE Hand Sanitizer Gel
NDC: 76709-203 | Form: GEL
Manufacturer: INVICTA ASIA CO., LTD
Category: otc | Type: HUMAN OTC DRUG LABEL
Date: 20200702

ACTIVE INGREDIENTS: ALCOHOL 70 mL/100 mL
INACTIVE INGREDIENTS: SCUTELLARIA BAICALENSIS ROOT; ALOE VERA LEAF; ALLANTOIN; GLYCERIN; CARBOMER HOMOPOLYMER, UNSPECIFIED TYPE; WATER

76709-203

Active ingredient

Ethyl Alcohol 70%

Purpose

Antimicrobial

Use

For handwashing to decrease bacteria on skin without soap and water. Recommended for repeated use.

Warnings

For external use only. Flammable, Keep away from fire or flame.

Do not use

in eyes. If this happens, rinse thoroughly with water.

Stop use and ask a doctor

if irritation and rash appears and lasts.

Keep out of reach of children.

If swallowed, get medical help or contact a Poison Control Center right away.

Directions

Wet hands & wrists thoroughly with product and allow to dry without wiping. Children under 6 years of age should be supervised while using this product.

Inactive ingredients

Aqua(Purified Water), Aloe Vera, Allantoin, Scutellaria Baicalensis Root Extract, Carbomer, Glycerin